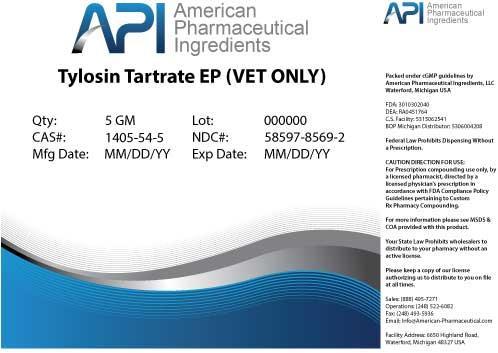 DRUG LABEL: Tylosin Tartrate
NDC: 58597-8569 | Form: POWDER
Manufacturer: AMERICAN PHARMACEUTICAL INGREDIENTS LLC
Category: other | Type: BULK INGREDIENT
Date: 20140502

ACTIVE INGREDIENTS: Tylosin Tartrate 1 g/1 g

Tylosin Tartrate